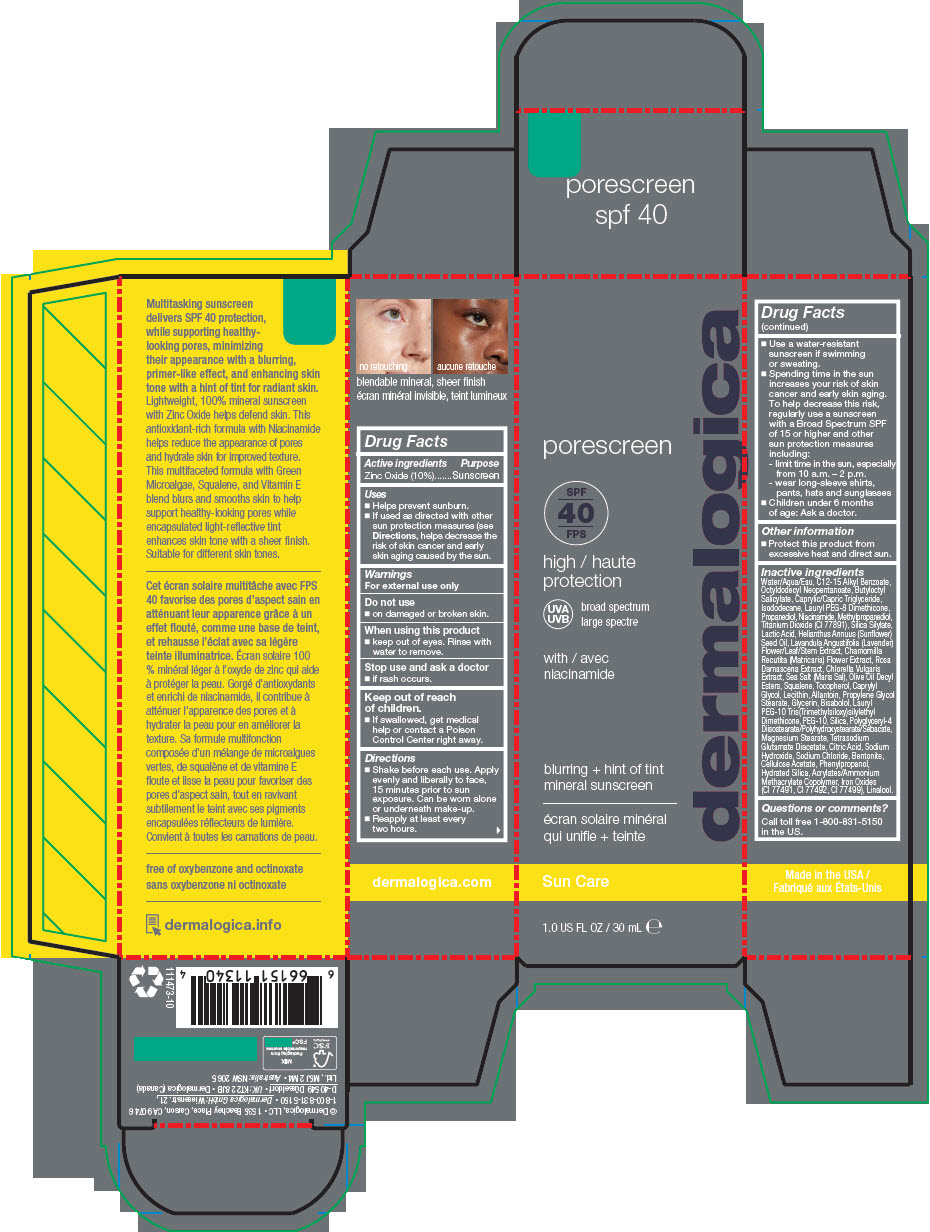 DRUG LABEL: PORESCREEN SPF40
NDC: 68479-291 | Form: LOTION
Manufacturer: Dermalogica, LLC.
Category: otc | Type: HUMAN OTC DRUG LABEL
Date: 20241227

ACTIVE INGREDIENTS: Zinc Oxide 10 mg/100 mL
INACTIVE INGREDIENTS: Water; ALKYL (C12-15) BENZOATE; Octyldodecyl Neopentanoate; Butyloctyl Salicylate; MEDIUM-CHAIN TRIGLYCERIDES; Isododecane; Propanediol; Methylpropanediol; Niacinamide; Titanium Dioxide; SILICON DIOXIDE; Polyglyceryl-4 Diisostearate/Polyhydroxystearate/Sebacate; Sodium Chloride; Bentonite; Caprylyl Glycol; FERROSOFERRIC OXIDE; FERRIC OXIDE RED; FERRIC OXIDE YELLOW; SUNFLOWER OIL; SOYBEAN LECITHIN; Allantoin; Cellulose Acetate; Olive Oil Decyl Esters; Phenylpropanol; PROPYLENE GLYCOL MONOSTEARATE; Magnesium Stearate; CITRIC ACID MONOHYDRATE; Glycerin; Hydrated Silica; POLYETHYLENE OXIDE 200000; Tetrasodium Glutamate Diacetate; LACTIC ACID, DL-; LAVANDULA ANGUSTIFOLIA SUBSP. ANGUSTIFOLIA FLOWERING TOP; LEVOMENOL; Squalene; MATRICARIA CHAMOMILLA WHOLE; ROSA X ALBA FLOWER OIL; CHLORELLA VULGARIS; Sea Salt; Sodium Hydroxide; Tocopherol; LINALOOL, (+/-)-

PORESCREEN SPF40

Drug Facts

Active ingredients

Zinc Oxide (10%)

Purpose

Sunscreen

Uses

- Helps prevent sunburn.
- If used as directed with other sun protection measures (see Directions, helps decrease the risk of skin cancer and early skin aging caused by the sun.

Warnings

For external use only

Do not use

- on damaged or broken skin.

When using this product

- keep out of eyes. Rinse with water to remove.

Stop use and ask a doctor

- if rash occurs.

Keep out of reach of children.

- If swallowed, get medical help or contact a Poison Control Center right away.

Directions

- Shake before each use. Apply evenly and liberally to face, 15 minutes prior to sun exposure. Can be worn alone or underneath make-up.
- Reapply at least every two hours.
- Use a water-resistant sunscreen if swimming or sweating.
- Spending time in the sun increases your risk of skin cancer and early skin aging. To help decrease this risk, regularly use a sunscreen with a Broad Spectrum SPF of 15 or higher and other sun protection measures including:
  - limit time in the sun, especially from 10 a.m. – 2 p.m.
  - wear long-sleeve shirts, pants, hats and sunglasses
- Children under 6 months of age: Ask a doctor.

Other information

- Protect this product from excessive heat and direct sun.

Inactive ingredients

Water/Aqua/Eau, C12-15 Alkyl Benzoate, Octyldodecyl Neopentanoate, Butyloctyl Salicylate, Caprylic/Capric Triglyceride, Isododecane, Lauryl PEG-8 Dimethicone, Propanediol, Niacinamide, Methylpropanediol, Titanium Dioxide (CI 77891), Silica Silylate, Lactic Acid, Helianthus Annuus (Sunflower) Seed Oil, Lavandula Angustifolia (Lavender) Flower/Leaf/Stem Extract, Chamomilla Recutita (Matricaria) Flower Extract, Rosa Damascena Extract, Chlorella Vulgaris Extract, Sea Salt (Maris Sal), Olive Oil Decyl Esters, Squalene, Tocopherol, Caprylyl Glycol, Lecithin, Allantoin, Propylene Glycol Stearate, Glycerin, Bisabolol, Lauryl PEG-10 Tris(Trimethylsiloxy)silylethyl Dimethicone, PEG-10, Silica, Polyglyceryl-4 Diisostearate/Polyhydroxystearate/Sebacate, Magnesium Stearate, Tetrasodium Glutamate Diacetate, Citric Acid, Sodium Hydroxide, Sodium Chloride, Bentonite, Cellulose Acetate, Phenylpropanol, Hydrated Silica, Acrylates/Ammonium Methacrylate Copolymer, Iron Oxides (CI 77491, CI 77492, CI 77499), Linalool.

Questions or comments?

Call toll free 1-800-831-5150 in the US.

PRINCIPAL DISPLAY PANEL - 30 mL Tube Carton

dermalogica

porescreen

SPF
40

high
protection

UVA
UVB

broad spectrum

with
niacinamide

blurring + hint of tint
mineral sunscreen

Sun Care

1.0 US FL OZ / 30 mL ℮